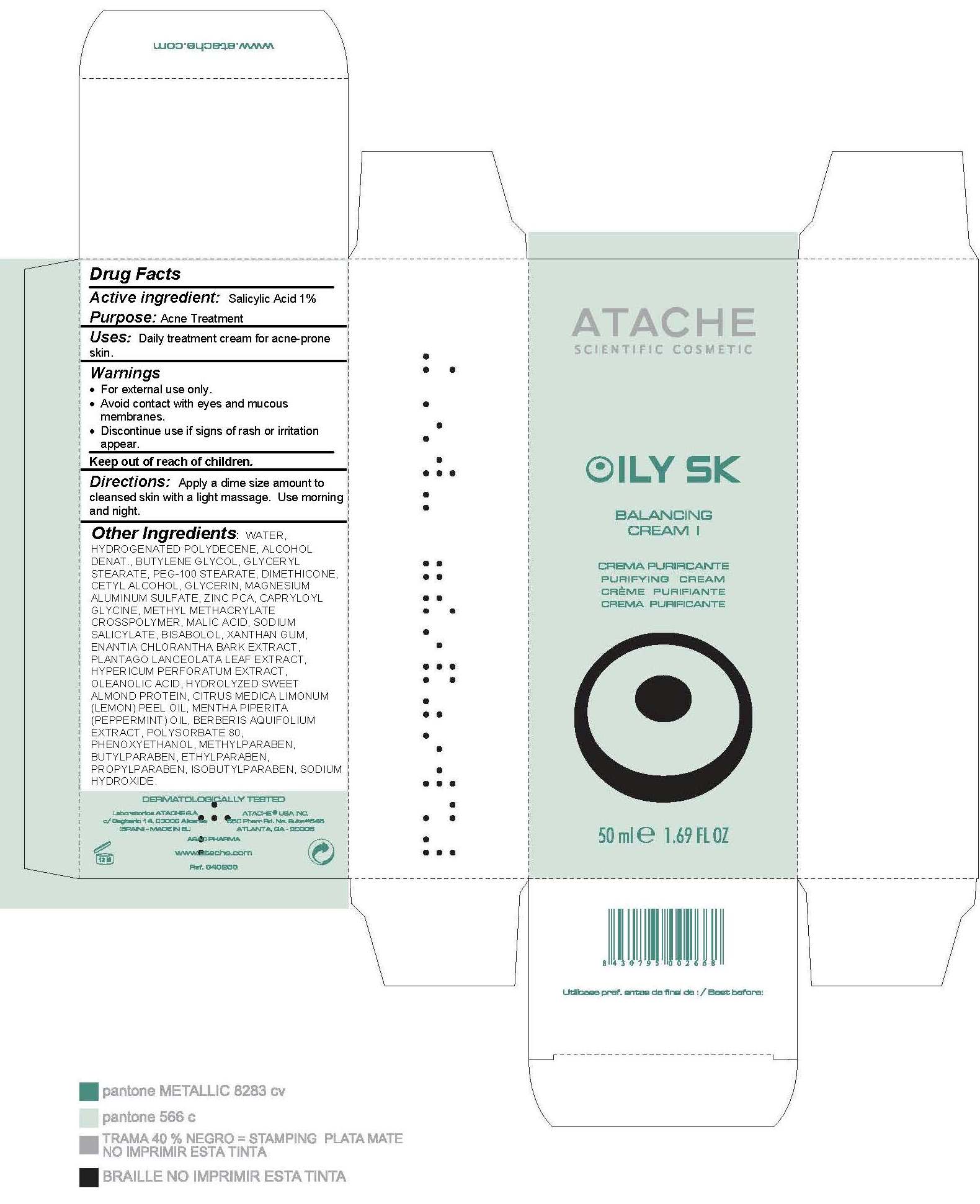 DRUG LABEL: Oily SK Balancing  I
NDC: 75870-009 | Form: CREAM
Manufacturer: LABORATORIOS DE COSMETICA SCIENTIFI
Category: otc | Type: HUMAN OTC DRUG LABEL
Date: 20110617

ACTIVE INGREDIENTS: SALICYLIC ACID .5 mL/50 mL
INACTIVE INGREDIENTS: WATER; HYDROGENATED POLYDECENE (550 MW); ALCOHOL; BUTYLENE GLYCOL; GLYCERYL MONOSTEARATE; PEG-100 STEARATE; DIMETHICONE; CETYL ALCOHOL; GLYCERIN; SULFURIC ACID; ZINC PIDOLATE; MAHONIA AQUIFOLIUM FRUITING TOP; ALOE VERA LEAF; MALIC ACID; SODIUM SALICYLATE; LEVOMENOL; XANTHAN GUM; ANNICKIA CHLORANTHA BARK; PLANTAGO LANCEOLATA LEAF; HYPERICUM PERFORATUM LEAF; OLEANOLIC ACID; ALMOND; LEMON OIL; PEPPERMINT OIL; MAHONIA AQUIFOLIUM FRUITING TOP; POLYSORBATE 80; PHENOXYETHANOL; METHYLPARABEN; BUTYLPARABEN; ETHYLPARABEN; PROPYLPARABEN; ISOBUTYLPARABEN; SODIUM HYDROXIDE

Drug Facts

Active Ingredient

Salicylic Acid 1%

Purpose: Acne Treatment

Keep out of reach of children.

INDICATIONS AND USAGE

Uses: Daily treatment cream for acne-prone skin.

Warnings:

- For external use only.
- Avoid contact with eyes and mucous membranes.
- Discontinue use if signs of rash or irrigation appear.

DOSAGE AND ADMINISTRATION

Directions: Apply a dime size amount to cleansed skin with a light massage. Use morning and night.

INACTIVE INGREDIENT

Other Ingredients: WATER, HYDROGENATED POLYDECENE, ALCOHOL DENAT., BUTYLENE GLYCOL, GLYCERYL STEARATE, PEG-100 STEARATE, DIMETHICONE, CETYL ALCOHOL, GLYCERIN, MAGNESIUM ALUMINUM SULFATE, ZINC PCA, CAPRYLOYL GLYCINE, METHYL METHACRYLATE CROSSPOLYMER, MALIC ACID, SODIUM SALICYLATE, BISABOLOL, XANTHAN GUM, ENANTIA CHLORANTHA BARK EXTRACT, PLANTAGO LANCEOLATA LEAF EXTRACT, HYPERICUM PERFORATUM EXTRACT, OLEANOLIC ACID, HYDROLYZED SWEET ALMOND PROTEIN, CITRUS MEDICA LIMONUM (LEMON) PEEL OIL, MENTHA PIPERITA (PEPPERMINT) OIL, BERBERIS AQUIFOLIUM EXTRACT, POLYSORBATE 80, PHENOXYETHANOL, METHYLPARABEN, BUTYLPARABEN, ETHYLPARABEN, PROPYLPARABEN, ISOBUTYLPARABEN, SODIUM HYDROXIDE.